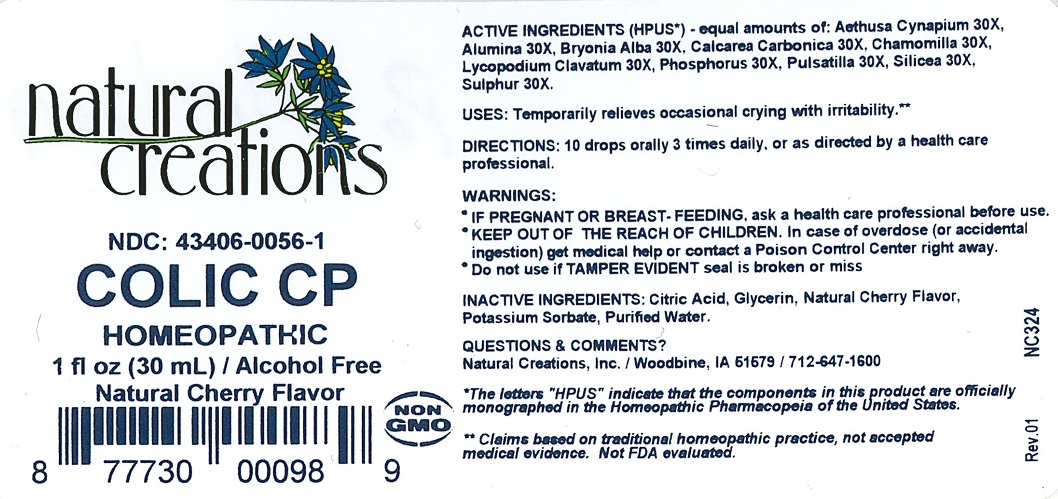 DRUG LABEL: COLIC CP
NDC: 43406-0056 | Form: LIQUID
Manufacturer: Natural Creations, Inc.
Category: homeopathic | Type: HUMAN OTC DRUG LABEL
Date: 20221219

ACTIVE INGREDIENTS: AETHUSA CYNAPIUM 30 [hp_X]/1 mL; ALUMINUM OXIDE 30 [hp_X]/1 mL; BRYONIA ALBA ROOT 30 [hp_X]/1 mL; OYSTER SHELL CALCIUM CARBONATE, CRUDE 30 [hp_X]/1 mL; MATRICARIA RECUTITA 30 [hp_X]/1 mL; LYCOPODIUM CLAVATUM SPORE 30 [hp_X]/1 mL; PHOSPHORUS 30 [hp_X]/1 mL; ANEMONE PULSATILLA 30 [hp_X]/1 mL; SILICON DIOXIDE 30 [hp_X]/1 mL; SULFUR 30 [hp_X]/1 mL
INACTIVE INGREDIENTS: CITRIC ACID ACETATE; GLYCERIN; POTASSIUM SORBATE; WATER

COLIC CP

ACTIVE INGREDIENT

ACTIVE INGREDIENTS (HPUS*) - equal amounts of: Aethusa Cynapium 30X, Alumina 30X, Bryonia Alba 30X, Calcarea Carbonica 30X, Chamomilla 30X, Lycopodium Clavatum 30X, Phosphorus 30X, Pulsatilla 30X, Silicea 30X, Sulphur 30X.

PURPOSE

USES: Temporarily relieves occasional crying with irritability.**

INDICATIONS AND USAGE

USES: Temporarily relieves occasional crying with irritability.**

DOSAGE AND ADMINISTRATION

DIRECTIONS: 10 drops orally 3 times daily, or as directed by a health care professional.

KEEP OUT OF REACH OF CHILDREN

KEEP OUT OF THE REACH OF CHILDREN. In case of overdose (or accidental ingestion) get medical help or contact a Poison Control Center right away.

WARNINGS:

- IF PREGNANT OR BREAST-FEEDING, ask a health care professional before use.
- KEEP OUT OF THE REACH OF CHILDREN. In case of overdose (or accidental ingestion) get medical help or contact a Poison Control Center right away.
- Do not use if TAMPER EVIDENT seal is broken or missing.

INACTIVE INGREDIENT

INACTIVE INGREDIENTS: Citric Acid, Glycerin, Natural Cherry Flavor, Potassium Sorbate, Purified Water.

QUESTIONS AND COMMENTS?

Natural Creations, Inc. / Woodbine, IA 51579 / 712-647-1600

REFERENCES

* The letters "HPUS" indicate the components in the product are officially monographed in the Homeopathic Pharmacopeia of the United States.

** Claims based on traditional homeopathic practice, not accepted medical evidence. Not FDA evaluated.

PACKAGE LABEL

NDC: 43406-0056-1

COLIC CP

HOMEOPATHIC

1 fl oz (30 mL) / 20% Alcohol